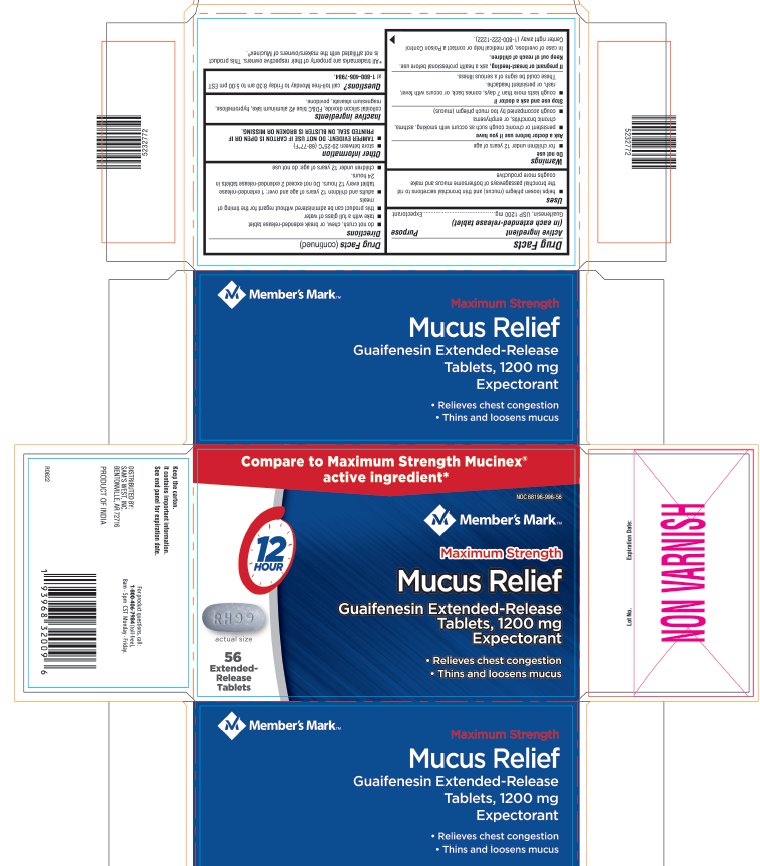 DRUG LABEL: Guaifenesin
NDC: 68196-996 | Form: TABLET, EXTENDED RELEASE
Manufacturer: SAM'S WEST INC
Category: otc | Type: HUMAN OTC DRUG LABEL
Date: 20220624

ACTIVE INGREDIENTS: Guaifenesin 1200 mg/1 1
INACTIVE INGREDIENTS: hypromellose, unspecified; magnesium stearate; silicon dioxide; povidone, unspecified; FD&C BLUE NO. 2

Guaifenesin
Extended Release

Drug Facts

Active ingredient (in each extended-release tablet)

Guaifenesin, USP 1200 mg

Purpose

Expectorant

Uses

- helps loosen phlegm (mucus) and thin bronchial secretions to rid the bronchial passageways of bothersome mucus and make coughs more productive

Warnings

Do not use

- for children under 12 years of age

Ask a doctor before use if you have

- persistent or chronic cough such as occurs with smoking, asthma, chronic bronchitis, or emphysema
- cough accompanied by too much phlegm (mucus)

Stop use and ask a doctor if

- cough lasts more than 7 days, comes back, or occurs with fever, rash, or persistent headache.
  These could be signs of a serious illness.

PREGNANCY OR BREAST FEEDING

If pregnant or breast-feeding, ask a health professional before use.

Keep out of reach of children.

In case of overdose, get medical help or contact a Poison Control Center right away (1-800-222-1222).

Directions

- do not crush, chew, or break extended-release tablet
- take with a full glass of water
- this product can be administered without regard for the timing of meals
- adults and children 12 years of age and over: 1 extended-release tablet every 12 hours. Do not exceed 2 extended-release tablets in 24 hours.
- children under 12 years of age: do not use

Other information

- store between 20-25°C (68-77°F)
- TAMPER EVIDENT: DO NOT USE IF CARTON IS OPEN OR IF PRINTED SEAL ON BLISTER IS BROKEN OR MISSING.

Inactive ingredients

colloidal silicon dioxide, FD&C blue #2 aluminum lake, hypromellose, magnesium stearate, povidone.

Questions?

call toll-free Monday to Friday 8:30 am to 5:00 pm EST at 1-800-406-7984.

DISTRIBUTED BY:
SAM'S WEST, INC.
BENTONVILLE, AR 72716

PRINCIPAL DISPLAY PANEL - 1200 mg Tablet Blister Pack Carton

Compare to Maximum Strength Mucinex®
active ingredient*

NDC 68196-996-56

Member's Mark™

Maximum Strength

Mucus Relief

Guaifenesin Extended-Release
Tablets, 1200 mg
Expectorant

- Relieves chest congestion
- Thins and loosens mucus

12
HOUR

56
Extended-
Release
Tablets